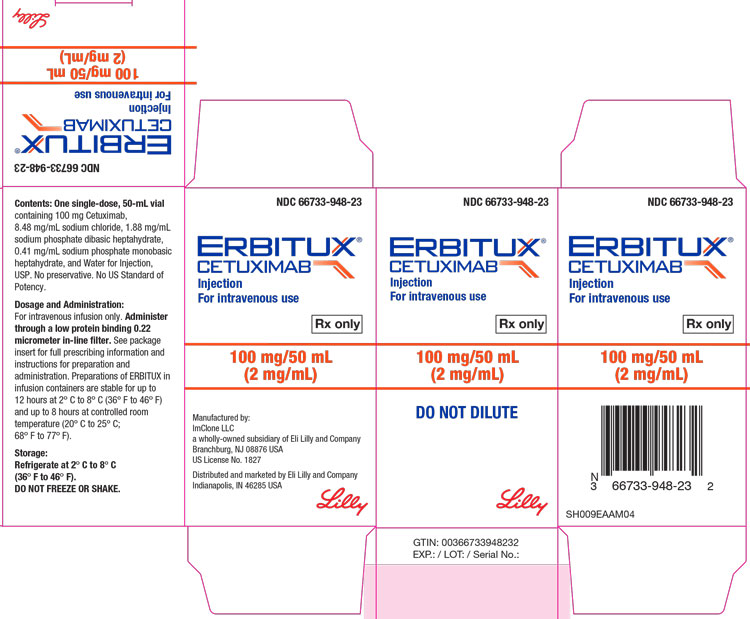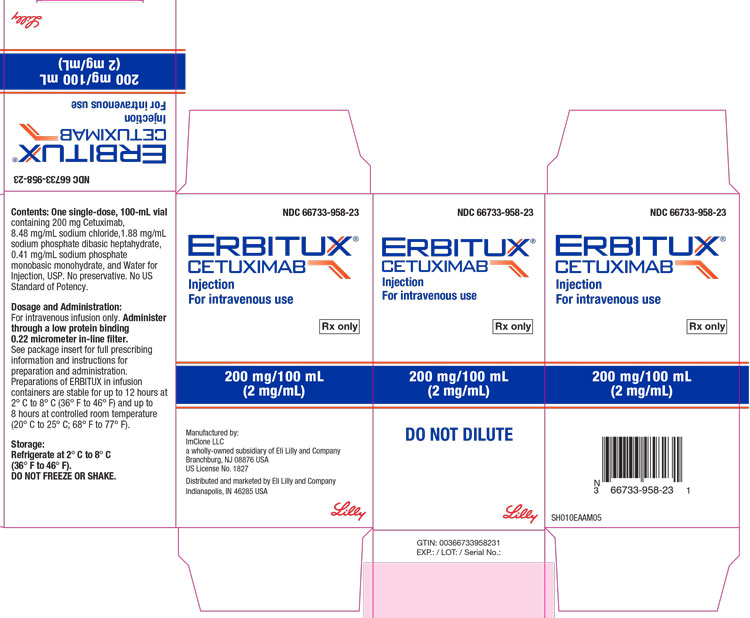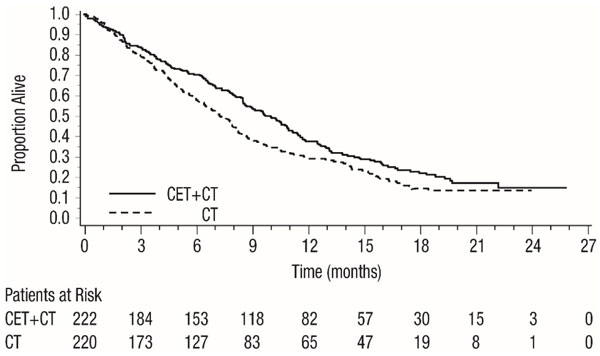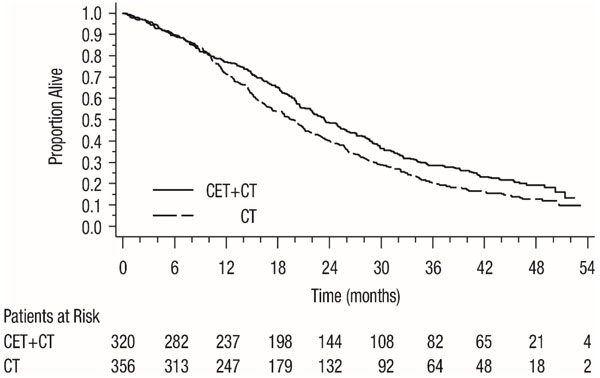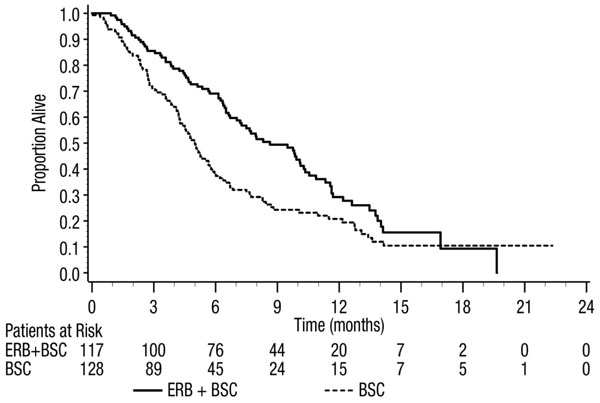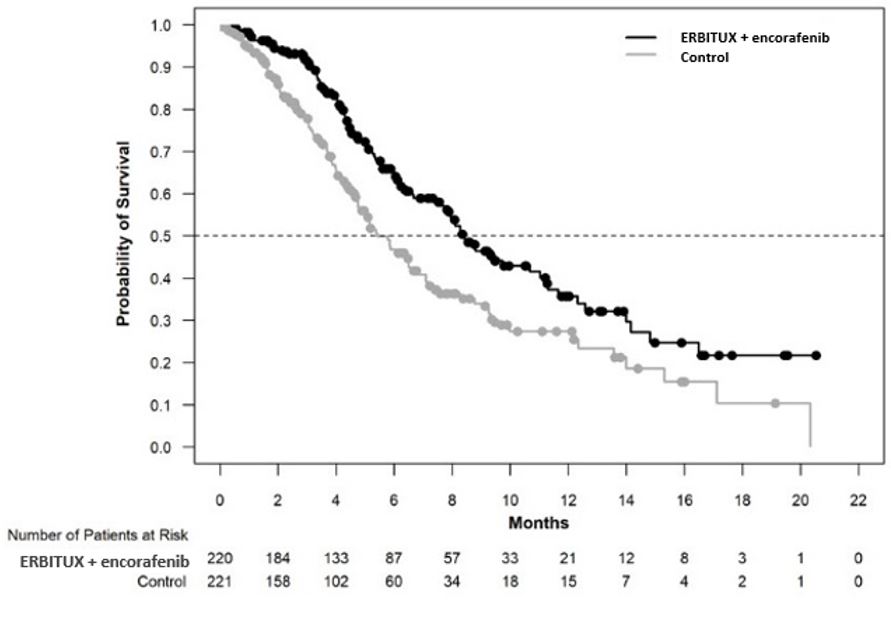 DRUG LABEL: ERBITUX
NDC: 66733-948 | Form: SOLUTION
Manufacturer: ImClone LLC
Category: prescription | Type: HUMAN PRESCRIPTION DRUG LABEL
Date: 20240725

ACTIVE INGREDIENTS: cetuximab 2 mg/1 mL
INACTIVE INGREDIENTS: SODIUM CHLORIDE 8.48 mg/1 mL; SODIUM PHOSPHATE, DIBASIC, HEPTAHYDRATE 1.88 mg/1 mL; SODIUM PHOSPHATE, MONOBASIC, MONOHYDRATE 0.41 mg/1 mL; SODIUM HYDROXIDE; HYDROCHLORIC ACID; WATER; Polysorbate 80

HIGHLIGHTS OF PRESCRIBING INFORMATION

These highlights do not include all the information needed to use ERBITUX safely and effectively. See full prescribing information for ERBITUX.
ERBITUX® (cetuximab) injection, for intravenous use
Initial U.S. Approval: 2004

RECENT MAJOR CHANGES

Indications and Usage (1.3) |  | 09/2021
Dosage and Administration
 | Recommended Dosage for Squamous Cell Carcinoma of the Head and Neck (SCCHN) (2.1) | 04/2021
 | Recommended Dosage for Colorectal Cancer (CRC) (2.2) | 04/2021
Dosage and Administration (2.1, 2.3) |  | 09/2021
Warnings and Precautions, Infusion Reactions (5.1) |  | 11/2020

WARNING: INFUSION REACTIONS and CARDIOPULMONARY ARREST

See full prescribing information for complete boxed warning.

- ERBITUX can cause serious and fatal infusion reactions. (5.1, 6) Immediately interrupt and permanently discontinue ERBITUX for serious infusion reactions. (2.5)
- Cardiopulmonary arrest or sudden death occurred in patients with squamous cell carcinoma of the head and neck receiving ERBITUX with radiation therapy or with a cetuximab product with platinum-based therapy and fluorouracil. Monitor serum electrolytes, including serum magnesium, potassium, and calcium, during and after ERBITUX administration. (5.2, 5.6)

1 INDICATIONS AND USAGE

ERBITUX® is an epidermal growth factor receptor (EGFR) antagonist indicated for treatment of:

Head and Neck Cancer

- Locally or regionally advanced squamous cell carcinoma of the head and neck in combination with radiation therapy. (1.1, 14.1)
- Recurrent locoregional disease or metastatic squamous cell carcinoma of the head and neck in combination with platinum-based therapy with fluorouracil. (1.1, 14.1)
- Recurrent or metastatic squamous cell carcinoma of the head and neck progressing after platinum-based therapy. (1.1, 14.1)

Colorectal Cancer

- K-Ras wild-type, EGFR-expressing, metastatic colorectal cancer as determined by an FDA-approved test
  - in combination with FOLFIRI for first-line treatment,
  - in combination with irinotecan in patients who are refractory to irinotecan-based chemotherapy,
  - as a single-agent in patients who have failed oxaliplatin- and irinotecan-based chemotherapy or who are intolerant to irinotecan. (1.2, 5.7, 12.1, 14.2)

Limitations of Use: ERBITUX is not indicated for treatment of Ras-mutant colorectal cancer or when the results of the Ras mutation tests are unknown. (5.7)

- BRAF V600E Mutation-Positive Metastatic Colorectal Cancer (CRC)
  - in combination with encorafenib, for the treatment of adult patients with metastatic colorectal cancer (CRC) with a BRAF V600E mutation, as detected by an FDA-approved test, after prior therapy. (1.3)

2 DOSAGE AND ADMINISTRATION

- Premedicate with an H1 receptor antagonist. (2.4)
- In Combination With Radiation Therapy:
  - Initial dose: 400 mg/m^2 administered as a 120-minute intravenous infusion one week prior to initiating a course of radiation therapy. (2.2)
  - Subsequent doses: 250 mg/m^2 administered as a 60-minute infusion every week for the duration of radiation therapy (6–7 weeks). (2.2)
  - Complete ERBITUX administration 1 hour prior to radiation therapy. (2.2)
- As Single-Agent or in Combination With Chemotherapy:
  - Weekly: Administer initial dose of 400 mg/m^2 as a 120-minute intravenous infusion, and subsequent doses of 250 mg/m^2 infused over 60 minutes once weekly. (2.2, 2.3)
  - Biweekly: Administer 500 mg/m^2 as a 120-minute intravenous infusion every two weeks. (2.2, 2.3)
  - Complete ERBITUX administration 1 hour prior to chemotherapy. Continue treatment until disease progression or unacceptable toxicity. (2.2, 2.3)
- See full prescribing information for dosage adjustments for adverse reactions. (2.5)

3 DOSAGE FORMS AND STRENGTHS

- Injection: 100 mg/50 mL (2 mg/mL) or 200 mg/100 mL (2 mg/mL) in a single-dose vial. (3)

4 CONTRAINDICATIONS

None. (4)

5 WARNINGS AND PRECAUTIONS

- Infusion Reactions: Monitor patients following infusion. Immediately stop and permanently discontinue ERBITUX for serious infusion reactions. (2.5, 5.1)
- Cardiopulmonary Arrest: Monitor serum electrolytes during and after ERBITUX. (5.2, 5.6)
- Pulmonary Toxicity: Interrupt or permanently discontinue for acute onset or worsening of pulmonary symptoms. (2.5, 5.3)
- Dermatologic Toxicity: Monitor for dermatologic toxicities or infectious sequelae. Limit sun exposure. (2.5, 5.4)
- Hypomagnesemia and Accompanying Electrolyte Abnormalities: Monitor during treatment and for at least 8 weeks following the completion. Replete electrolytes as necessary. (5.6)
- Increased tumor progression, increased mortality, or lack of benefit observed in patients with Ras-mutant mCRC. (5.7)
- Embryo-Fetal Toxicity: Can cause fetal harm. Advise females of potential risk to the fetus and to use effective contraception. (5.8, 8.1, 8.3)

6 ADVERSE REACTIONS

The most common adverse reactions (incidence ≥25%) with Erbitux as a single-agent or in combination with radiotherapy or chemotherapy (FOLFIRI, Irinotecan and 5-Fluorouracil/Platinum) are: cutaneous adverse reactions (including rash, pruritus, and nail changes), headache, diarrhea, and infection. (6)

The most common adverse reactions (>25%) for ERBITUX, in combination with encorafenib, are fatigue, nausea, diarrhea, dermatitis acneiform, abdominal pain, decreased appetite, arthralgia, and rash. (6).

To report SUSPECTED ADVERSE REACTIONS, contact Eli Lilly and Company at 1-800-LillyRx (1-800-545-5979) or FDA at 1-800-FDA-1088 or www.fda.gov/medwatch.

8 USE IN SPECIFIC POPULATIONS

- Lactation: Advise not to breastfeed. (8.2)

FULL PRESCRIBING INFORMATION

WARNING: INFUSION REACTIONS and CARDIOPULMONARY ARREST

Infusion Reactions: ERBITUX can cause serious and fatal infusion reactions [see Warnings and Precautions (5.1), Adverse Reactions (6)]. Immediately interrupt and permanently discontinue ERBITUX for serious infusion reactions [see Dosage and Administration (2.5)].

Cardiopulmonary Arrest: Cardiopulmonary arrest or sudden death occurred in patients with squamous cell carcinoma of the head and neck receiving ERBITUX with radiation therapy or a cetuximab product with platinum-based therapy and fluorouracil. Monitor serum electrolytes, including serum magnesium, potassium, and calcium, during and after ERBITUX administration [see Warnings and Precautions (5.2, 5.6)].

1 INDICATIONS AND USAGE

1.1 Squamous Cell Carcinoma of the Head and Neck (SCCHN)

ERBITUX® is indicated:

- in combination with radiation therapy for the initial treatment of locally or regionally advanced squamous cell carcinoma of the head and neck (SCCHN).
- in combination with platinum-based therapy with fluorouracil for the first-line treatment of patients with recurrent locoregional disease or metastatic SCCHN.
- as a single-agent for the treatment of patients with recurrent or metastatic SCCHN for whom prior platinum-based therapy has failed.

1.2 K-Ras Wild-type, EGFR-expressing Colorectal Cancer (CRC)

ERBITUX is indicated for the treatment of K-Ras wild-type, epidermal growth factor receptor (EGFR)-expressing, metastatic colorectal cancer (mCRC) as determined by an FDA-approved test [see Dosage and Administration (2.2)]:

- in combination with FOLFIRI (irinotecan, fluorouracil, leucovorin) for first-line treatment,
- in combination with irinotecan in patients who are refractory to irinotecan-based chemotherapy,
- as a single-agent in patients who have failed oxaliplatin- and irinotecan-based chemotherapy or who are intolerant to irinotecan.

Limitations of Use: ERBITUX is not indicated for treatment of Ras-mutant colorectal cancer or when the results of the Ras mutation tests are unknown [see Warnings and Precautions (5.7)].

1.3 BRAF V600E Mutation-Positive Metastatic Colorectal Cancer (CRC)

ERBITUX is indicated, in combination with encorafenib, for the treatment of adult patients with metastatic colorectal cancer (CRC) with a BRAF V600E mutation, as detected by an FDA-approved test, after prior therapy [see Dosage and Administration (2.3)].

2 DOSAGE AND ADMINISTRATION

2.1 Patient Selection

Select patients with metastatic colorectal cancer (CRC) for treatment with ERBITUX based on the presence of:

- Ras wild-type, EGFR-expressing CRC [see Clinical Studies (14.2)], or
- BRAF V600E mutation-positive metastatic CRC [see Clinical Studies (14.3)]

Information on FDA-approved tests for the detection of K-Ras or BRAF V600E mutations in CRC in patients with metastatic CRC is available at: http://www.fda.gov/CompanionDiagnostics.

2.2 Recommended Dosage for Squamous Cell Carcinoma of the Head and Neck (SCCHN)

In combination with radiation therapy

- Initial dose: 400 mg/m^2 administered as a 120-minute intravenous infusion one week prior to initiating a course of radiation therapy.
- Subsequent doses: 250 mg/m^2 administered as a 60-minute infusion every week for the duration of radiation therapy (6–7 weeks).
- Complete ERBITUX administration 1 hour prior to radiation therapy.

As a single-agent or in combination with platinum-based therapy and fluorouracil

Administer Erbitux as a single-agent or in combination with platinum-based therapy and fluorouracil on a weekly or biweekly schedule.

Weekly Dosage

- Initial dose: 400 mg/m^2 administered as a 120-minute intravenous infusion
- Subsequent doses: 250 mg/m^2 administered as a 60-minute infusion every week

Biweekly Dosage

- Initial and subsequent doses: 500 mg/m^2 administered as a 120-minute intravenous infusion every 2 weeks

Complete ERBITUX administration 1 hour prior to platinum-based therapy with fluorouracil. Continue treatment until disease progression or unacceptable toxicity.

2.3 Recommended Dosage for Colorectal Cancer (CRC)

As a single-agent or in combination with irinotecan or FOLFIRI (irinotecan, fluorouracil, leucovorin)

Administer Erbitux as a single-agent or in combination with irinotecan or FOLFIRI (irinotecan, fluorouracil, leucovorin) on a weekly or biweekly schedule.

Weekly Dosage

- Initial dose: 400 mg/m^2 administered as a 120-minute intravenous infusion
- Subsequent doses: 250 mg/m^2 administered as a 60-minute infusion every week

Biweekly Dosage

- Initial and subsequent doses: 500 mg/m^2 administered as a 120-minute intravenous infusion every 2 weeks

Complete ERBITUX administration 1 hour prior to irinotecan or FOLFIRI. Continue treatment until disease progression or unacceptable toxicity.

In combination with encorafenib

- The recommended initial dose is 400 mg/m^2 administered as a 120-minute intravenous infusion in combination with encorafenib.
- The recommended subsequent dosage is 250 mg/m^2 weekly as a 60-minute infusion in combination with encorafenib until disease progression or unacceptable toxicity.

Refer to the encorafenib prescribing information for recommended encorafenib dosage information.

2.4 Premedication

Premedicate with a histamine-1 (H1) receptor antagonist intravenously 30–60 minutes prior to the first dose or subsequent doses as deemed necessary [see Warnings and Precautions (5.1)].

2.5 Dosage Modifications for Adverse Reactions

Reduce, delay, or discontinue ERBITUX to manage adverse reactions as described in Table 1.

Table 1: Recommended Dosage Modifications for Adverse Reactions
Adverse Reaction | Severitya | Dosage Modification
Infusion reactions [see Warnings and Precautions (5.1)] | Grade 1 or 2 | Reduce the infusion rate by 50%.
Infusion reactions [see Warnings and Precautions (5.1)] | Grade 3 or 4 | Immediately and permanently, discontinue ERBITUX.
Dermatologic toxicities and infectious sequelae (e.g., acneiform rash, mucocutaneous disease) [see Warnings and Precautions (5.4)] | 1st occurrence; Grade 3 or 4 | Delay infusion 1 to 2 weeks; if condition improves, continue at 250 mg/m^2. If no improvement, discontinue ERBITUX.
Dermatologic toxicities and infectious sequelae (e.g., acneiform rash, mucocutaneous disease) [see Warnings and Precautions (5.4)] | 2nd occurrence; Grade 3 or 4 | Delay infusion 1 to 2 weeks; if condition improves, continue at 200 mg/m^2. If no improvement, discontinue ERBITUX.
Dermatologic toxicities and infectious sequelae (e.g., acneiform rash, mucocutaneous disease) [see Warnings and Precautions (5.4)] | 3rd occurrence; Grade 3 or 4 | Delay infusion 1 to 2 weeks; if condition improves, continue at 150 mg/m^2. If no improvement, discontinue ERBITUX.
Dermatologic toxicities and infectious sequelae (e.g., acneiform rash, mucocutaneous disease) [see Warnings and Precautions (5.4)] | 4th occurrence; Grade 3 or 4 | Discontinue ERBITUX.
Pulmonary toxicity [see Warnings and Precautions (5.3)] | Acute onset or worsening pulmonary symptoms | Delay infusion 1 to 2 weeks; if condition improves, continue at the dose that was being administered at the time of occurrence. If no improvement in 2 weeks or interstitial lung disease (ILD) is confirmed, discontinue ERBITUX.
a National Cancer Institute (NCI) Common Toxicity Criteria (CTC), version 2.0.

2.6 Preparation for Administration

- The solution should be clear and colorless and may contain a small amount of easily visible, white, amorphous, cetuximab particulates. Do not shake or dilute.
- Visually inspect for foreign particulate matter and discoloration prior to administration, whenever solution and container permit. Do not use if solution is discolored, cloudy, or contains foreign particulate matter.
- Do not administer ERBITUX as an intravenous push or bolus.
- Administer via infusion pump or syringe pump. Do not exceed an infusion rate of 10 mg/min.
- Administer through a low protein binding 0.22-micrometer in-line filter.

3 DOSAGE FORMS AND STRENGTHS

Injection: 100 mg/50 mL (2 mg/mL) or 200 mg/100 mL (2 mg/mL) as a clear, colorless solution in a single-dose vial.

4 CONTRAINDICATIONS

None.

5 WARNINGS AND PRECAUTIONS

5.1 Infusion Reactions

ERBITUX can cause serious and fatal infusion reactions. Infusion reactions of any grade occurred in 8.4% of 1373 patients who received ERBITUX across clinical trials. Severe (Grades 3 and 4) infusion reactions occurred in 2.2% of patients [see Adverse Reactions (6.1)]. Signs and symptoms included rapid onset of airway obstruction (bronchospasm, stridor, hoarseness), hypotension, shock, loss of consciousness, myocardial infarction, and/or cardiac arrest.

The risk of anaphylactic reactions may be increased in patients with a history of tick bites, red meat allergy, or in the presence of IgE antibodies directed against galactose-α-1,3-galactose (alpha-gal). Consider testing patients for alpha-gal IgE antibodies using FDA-cleared methods prior to initiating ERBITUX. Negative results for alpha-gal antibodies do not rule out the risk of severe infusion reactions.

Approximately 90% of severe infusion reactions occurred with the first infusion despite premedication with antihistamines. Infusion reactions may occur during or several hours following completion of the infusion.

Premedicate with a histamine-1(H1) receptor antagonist as recommended [see Dosage and Administration (2.4)]. Monitor patients for at least 1 hour following each ERBITUX infusion, in a setting with resuscitation equipment and other agents necessary to treat anaphylaxis. In patients requiring treatment for infusion reactions, monitor for more than 1 hour to confirm resolution of the reaction. Interrupt the infusion and upon recovery, resume the infusion at a slower rate or permanently discontinue ERBITUX based on severity [see Dosage and Administration (2.5)].

5.2 Cardiopulmonary Arrest

ERBITUX can cause cardiopulmonary arrest. Cardiopulmonary arrest or sudden death occurred in 2% of 208 patients treated with radiation therapy and ERBITUX in BONNER. Three patients with prior history of coronary artery disease died at home, with myocardial infarction as the presumed cause of death. One of these patients had arrhythmia and one had congestive heart failure. Death occurred 27, 32, and 43 days after the last dose of ERBITUX. One patient with no prior history of coronary artery disease died one day after the last dose of ERBITUX.

In EXTREME, fatal cardiac disorders and/or sudden death occurred in 3% of 219 patients treated with a cetuximab product in combination with platinum-based therapy and fluorouracil.

Carefully consider use of ERBITUX with radiation therapy or platinum-based therapy with fluorouracil in patients with SCCHN with a history of coronary artery disease, congestive heart failure, or arrhythmias. Monitor serum electrolytes, including serum magnesium, potassium, and calcium, during and after ERBITUX [see Warnings and Precautions (5.6)].

5.3 Pulmonary Toxicity

ERBITUX can cause interstitial lung disease (ILD). ILD, including 1 fatality, occurred in <0.5% of 1570 patients receiving ERBITUX in clinical trials.

Monitor patients for signs and symptoms of pulmonary toxicity. Interrupt or permanently discontinue ERBITUX for acute onset or worsening of pulmonary symptoms. Permanently discontinue ERBITUX for confirmed ILD [see Dosage and Administration (2.5)].

5.4 Dermatologic Toxicity

ERBITUX can cause dermatologic toxicities, including acneiform rash, skin drying and fissuring, paronychial inflammation, infectious sequelae (for example, S. aureus sepsis, abscess formation, cellulitis, blepharitis, conjunctivitis, keratitis/ulcerative keratitis with decreased visual acuity, cheilitis), and hypertrichosis.

Acneiform rash occurred in 82% of the 1373 patients who received ERBITUX across clinical trials. Severe (Grades 3 or 4) acneiform rash occurred in 10% of patients [see Adverse Reactions (6.1)]. Acneiform rash usually developed within the first two weeks of therapy; the rash lasted more than 28 days after stopping ERBITUX in most patients.

Life-threatening and fatal bullous mucocutaneous disease with blisters, erosions, and skin sloughing, has been observed in patients who received ERBITUX. It could not be determined whether these mucocutaneous adverse reactions were directly related to EGFR inhibition or to idiosyncratic immune-related effects (e.g., Stevens-Johnson syndrome or toxic epidermal necrolysis).

Monitor patients receiving ERBITUX for dermatologic toxicities and infectious sequelae. Instruct patients to limit sun exposure during ERBITUX therapy. Withhold, reduce dose or permanently discontinue ERBITUX based on severity of acneiform rash or mucocutaneous disease [see Dosage and Administration (2.5)].

5.5 Risks Associated with Use in Combination with Radiation and Cisplatin

In a controlled study, 940 patients with locally advanced SCCHN were randomized 1:1 to receive either ERBITUX in combination with radiation therapy and cisplatin or radiation therapy and cisplatin alone. The addition of ERBITUX resulted in an increase in the incidence of Grade 3 and 4 mucositis, radiation recall syndrome, acneiform rash, cardiac events, and electrolyte disturbances compared to radiation and cisplatin alone. Adverse reactions with fatal outcome were reported in 4% of patients in the ERBITUX combination arm and 3% in the control arm. In the ERBITUX arm, 2% experienced myocardial ischemia compared to 0.9% in the control arm. The main efficacy outcome of the study was progression-free survival (PFS). The addition of ERBITUX to radiation and cisplatin did not improve PFS. ERBITUX is not indicated for the treatment of SCCHN in combination with radiation and cisplatin.

5.6 Hypomagnesemia and Accompanying Electrolyte Abnormalities

ERBITUX can cause hypomagnesemia. Hypomagnesemia occurred in 55% of 365 patients receiving ERBITUX in Study CA225-025 and two other clinical trials in patients with colorectal cancer (CRC) or head and neck cancer, including Grades 3 and 4 in 6% to 17%.

In EXTREME, where a cetuximab product was administered in combination with platinum-based therapy, the addition of cetuximab to cisplatin and fluorouracil resulted in an increased incidence of hypomagnesemia of any grade (14%) and of Grade 3 or 4 hypomagnesemia (7%). Hypomagnesemia of any grade occurred in 4% of patients who received cetuximab, carboplatin, and fluorouracil. No patient experienced Grade 3 or 4 hypomagnesemia [see Adverse Reactions (6.1)].

Hypomagnesemia and accompanying electrolyte abnormalities can occur days to months after initiating ERBITUX. Monitor patients weekly during treatment for hypomagnesemia, hypocalcemia, and hypokalemia, and for at least 8 weeks following the completion of ERBITUX. Replete electrolytes as necessary.

5.7 Increased Tumor Progression, Increased Mortality, or Lack of Benefit in Patients with Ras-Mutant mCRC

ERBITUX is not indicated for the treatment of patients with CRC that harbor somatic mutations in exon 2 (codons 12 and 13), exon 3 (codons 59 and 61), and exon 4 (codons 117 and 146) of either K-Ras or N-Ras and hereafter is referred to as “Ras” or when the Ras status is unknown.

Retrospective subset analyses of Ras-mutant and wild-type populations across several randomized clinical trials, including CRYSTAL, were conducted to investigate the role of Ras mutations on the clinical effects of anti-EGFR-directed monoclonal antibodies. Use of cetuximab in patients with Ras mutations resulted in no clinical benefit with treatment related toxicity. Confirm Ras mutation status in tumor specimens prior to initiating ERBITUX [see Indications and Usage (1.2)].

5.8 Embryo-Fetal Toxicity

Based on animal data and its mechanism of action, ERBITUX can cause fetal harm when administered to a pregnant woman. There are no available data for ERBITUX exposure in pregnant women. In an animal reproduction study, intravenous administration of cetuximab once weekly to pregnant cynomolgus monkeys during the period of organogenesis resulted in an increased incidence of embryolethality and abortion. Disruption or depletion of EGFR in animal models results in impairment of embryo-fetal development including effects on placental, lung, cardiac, skin, and neural development. Advise pregnant women of the potential risk to a fetus. Advise females of reproductive potential to use effective contraception during treatment with ERBITUX and for 2 months after the last dose of ERBITUX [see Use in Specific Populations (8.1, 8.3)].

6 ADVERSE REACTIONS

The following adverse reactions are discussed in greater detail in other sections of the label:

- Infusion reactions [see Warnings and Precautions (5.1)].
- Cardiopulmonary arrest [see Warnings and Precautions (5.2)].
- Pulmonary toxicity [see Warnings and Precautions (5.3)].
- Dermatologic toxicity [see Warnings and Precautions (5.4)].
- Hypomagnesemia and Electrolyte Abnormalities [see Warnings and Precautions (5.6)].

6.1 Clinical Trials Experience

Because clinical trials are conducted under widely varying conditions, adverse reaction rates observed in the clinical trials of a drug cannot be directly compared to rates in the clinical trials of another drug and may not reflect the rates observed in practice.

The data described in Warnings and Precautions reflect exposure to ERBITUX in 1373 patients with SCCHN or CRC enrolled in clinical trials and treated at the recommended dosage for a median of 7 to 14 weeks [see Clinical Studies (14.1, 14.2)]. The most common adverse reactions in clinical trials with ERBITUX as a single-agent or in combination with radiotherapy or chemotherapy [FOLFIRI, irinotecan and 5-fluorouracil/platinum] (incidence ≥25%) include cutaneous adverse reactions (including rash, pruritus, and nail changes), headache, diarrhea, and infection.

Squamous Cell Carcinoma of the Head and Neck (SCCHN)

In Combination with Radiation Therapy

The safety of ERBITUX in combination with radiation therapy compared to radiation therapy alone was evaluated in BONNER. The data described below reflect exposure to ERBITUX in 420 patients with locally or regionally advanced SCCHN. ERBITUX was administered at the recommended dosage (400 mg/m^2 initial dose, followed by 250 mg/m^2 weekly). Patients received a median of 8 infusions (range 1 to 11) [see Clinical Studies (14.1)].

Table 2 provides the frequency and severity of adverse reactions in BONNER.

Table 2: Selected Adverse Reactions in ≥10% of Patients with Locoregionally Advanced SCCHN (BONNER)a
Adverse Reaction | ERBITUX with Radiation (n=208) |  | Radiation Therapy Alone (n=212)
Adverse Reaction | Grades 1–4 b | Grades 3 and 4 | Grades 1–4 | Grades 3 and 4
General
Asthenia | 56 | 4 | 49 | 5
Feverc | 29 | 1 | 13 | 1
Headache | 19 | <1 | 8 | <1
Chillsc | 16 | 0 | 5 | 0
Infusion Reactiond | 15 | 3 | 2 | 0
Infection | 13 | 1 | 9 | 1
Gastrointestinal
Nausea | 49 | 2 | 37 | 2
Emesis | 29 | 2 | 23 | 4
Diarrhea | 19 | 2 | 13 | 1
Dyspepsia | 14 | 0 | 9 | 1
Metabolism and Nutrition
Weight Loss | 84 | 11 | 72 | 7
Dehydration | 25 | 6 | 19 | 8
Increased Alanine Transaminasee | 43 | 2 | 21 | 1
Increased Aspartate Transaminasee | 38 | 1 | 24 | 1
Increased Alkaline Phosphatasee | 33 | <1 | 24 | 0
Respiratory
Pharyngitis | 26 | 3 | 19 | 4
Dermatologic
Acneiform Rashf | 87 | 17 | 10 | 1
Radiation Dermatitis | 86 | 23 | 90 | 18
Application Site Reaction | 18 | 0 | 12 | 1
Pruritus | 16 | 0 | 4 | 0
a Adverse reactions occurring in ≥10% of patients in the ERBITUX combination arm and at a higher incidence (≥5%) compared to the radiation alone arm.
b Adverse reactions were graded using the NCI CTC, version 2.0.
c Includes cases also reported as infusion reaction.
d Infusion reaction defined as any event described at any time during the clinical study as “allergic reaction” or “anaphylactoid reaction”, or any event occurring on the first day of dosing described as “allergic reaction”, “anaphylactoid reaction”, “fever”, “chills”, “chills and fever”, or “dyspnea”.
e Based on laboratory measurements, not on reported adverse reactions, the number of subjects with tested samples varied from 205–206 for ERBITUX with Radiation arm; 209–210 for Radiation alone.
f Acneiform rash defined as any event described as “acne”, “rash”, “maculopapular rash”, “pustular rash”, “dry skin”, or “exfoliative dermatitis”.

The overall incidence of late radiation toxicities (any grade) was higher for patients receiving ERBITUX in combination with radiation therapy compared with radiation therapy alone. The following sites were affected: salivary glands (65% versus 56%), larynx (52% versus 36%), subcutaneous tissue (49% versus 45%), mucous membrane (48% versus 39%), esophagus (44% versus 35%), skin (42% versus 33%). The incidence of Grade 3 or 4 late radiation toxicities was similar between the radiation therapy alone and the ERBITUX with radiation treatment groups.

In Combination with Platinum-based Therapy and Fluorouracil

The safety of a cetuximab product in combination with platinum-based therapy and fluorouracil or platinum-based therapy and fluorouracil alone was evaluated in EXTREME. The data described below reflect exposure to a cetuximab product in 434 patients with recurrent locoregional disease or metastatic SCCHN. Because ERBITUX provides approximately 22% higher exposure relative to the cetuximab product, the data provided below may underestimate the incidence and severity of adverse reactions anticipated with ERBITUX for this indication; however, the tolerability of the recommended dose is supported by safety data from additional studies of ERBITUX [see Clinical Pharmacology (12.3)]. Cetuximab was administered intravenously at a dosage of 400 mg/m^2 for the initial dose, followed by 250 mg/m^2 weekly. Patients received a median of 17 infusions (range 1 to 89) [see Clinical Studies (14.1)].

Table 3 provides the frequency and severity of adverse reactions in EXTREME.

Table 3: Selected Adverse Reactions in ≥10% of Patients with Recurrent Locoregional Disease or Metastatic SCCHN (EXTREME)a
Adverse Reaction | Cetuximab with Platinum-based Therapy and fluorouracil (n=219) |  | Platinum-based Therapy and fluorouracil Alone (n=215)
Adverse Reaction | Grades 1–4b | Grades 3 and 4 | Grades 1–4 | Grades 3 and 4
Eye
Conjunctivitis | 10 | 0 | 0 | 0
Gastrointestinal
Nausea | 54 | 4 | 47 | 4
Diarrhea | 26 | 5 | 16 | 1
General and Administration Site
Pyrexia | 22 | 0 | 13 | 1
Infusion Reactionc | 10 | 2 | <1 | 0
Infections
Infectiond | 44 | 11 | 27 | 8
Metabolism and Nutrition
Anorexia | 25 | 5 | 14 | 1
Hypocalcemia | 12 | 4 | 5 | 1
Hypokalemia | 12 | 7 | 7 | 5
Hypomagnesemia | 11 | 5 | 5 | 1
Dermatologic
Acneiform Rashe | 70 | 9 | 2 | 0
Rash | 28 | 5 | 2 | 0
Acne | 22 | 2 | 0 | 0
Dermatitis Acneiform | 15 | 2 | 0 | 0
Dry Skin | 14 | 0 | <1 | 0
Alopecia | 12 | 0 | 7 | 0
a Adverse reactions occurring in ≥10% of patients in the cetuximab combination arm and at a higher incidence (≥5%) compared to the platinum-based therapy and fluorouracil alone arm.
b Adverse reactions were graded using the NCI CTC, version 2.0.
c Infusion reaction defined as “anaphylactic reaction”, “hypersensitivity”, “fever and/or chills”, “dyspnea”, or “pyrexia” on the first day of dosing.
d Infection excludes sepsis-related events which are presented separately.
e Acneiform rash defined as “acne”, “dermatitis acneiform”, “dry skin”, “exfoliative rash”, “rash”, “rash erythematous”, “rash macular”, “rash papular”, or “rash pustular”.
Chemotherapy = cisplatin and fluorouracil or carboplatin and fluorouracil

For cardiac disorders, approximately 9% of patients in both treatment arms in EXTREME experienced a cardiac event. The majority of these events occurred in patients who received cisplatin and fluorouracil with or without cetuximab. Cardiac disorders were observed in 11% and 12% of patients who received cisplatin and fluorouracil with or without cetuximab, respectively, and 6% and 4% in patients who received carboplatin and fluorouracil with or without cetuximab, respectively. In both arms, the incidence of cardiovascular events was higher in the cisplatin and fluorouracil containing subgroup. Death attributed to cardiovascular events or sudden death was reported in 3% of the patients in the cetuximab with platinum-based therapy and fluorouracil arm and in 2% of the patients in the platinum-based therapy and fluorouracil alone arm.

K-Ras Wild-type, EGFR-expressing, Metastatic Colorectal Cancer (mCRC)

In Combination with FOLFIRI

The safety of a cetuximab product in combination with FOLFIRI or FOLFIRI alone was evaluated in CRYSTAL. The data described below reflect exposure to a cetuximab product in 667 patients with K-Ras wild-type, EGFR-expressing, mCRC. ERBITUX provides approximately 22% higher exposure compared to this product; however, the safety data from CRYSTAL is consistent in incidence and severity of adverse reactions with those seen for ERBITUX in this indication. Cetuximab was administered intravenously at a dosage of 400 mg/m^2 initial dose, followed by 250 mg/m^2 weekly. Patients received a median of 24 infusions (range 1 to 224) [see Clinical Studies (14.2)].

Serious adverse reactions included pulmonary embolism, which was reported in 4.4% of patients treated with cetuximab with FOLFIRI as compared to 3.4% of patients treated with FOLFIRI alone.

Table 4 provides the frequency and severity of adverse reactions in CRYSTAL.

Table 4: Selected Adverse Reactions in ≥10% of Patients with K-Ras Wild-type and EGFR-expressing, Metastatic Colorectal Cancer (CRYSTAL)a
Adverse Reaction | Cetuximab with FOLFIRI (n=317) |  | FOLFIRI Alone (n=350)
Adverse Reaction | Grades 1–4 b | Grades 3 and 4 | Grades 1–4 | Grades 3 and 4
Hematologic
Neutropenia | 49 | 31 | 42 | 24
Eye
Conjunctivitis | 18 | <1 | 3 | 0
Gastrointestinal
Diarrhea | 66 | 16 | 60 | 10
Stomatitis | 31 | 3 | 19 | 1
Dyspepsia | 16 | 0 | 9 | 0
General and Administration Site
Pyrexia | 26 | 1 | 14 | 1
Weight Decreased | 15 | 1 | 9 | 1
Infusion Reactionc | 14 | 2 | <1 | 0
Infections
Paronychia | 20 | 4 | <1 | 0
Metabolism and Nutrition
Anorexia | 30 | 3 | 23 | 2
Dermatologic
Acne-like Rashd | 86 | 18 | 13 | <1
Rash | 44 | 9 | 4 | 0
Dermatitis Acneiform | 26 | 5 | <1 | 0
Dry Skin | 22 | 0 | 4 | 0
Acne | 14 | 2 | 0 | 0
Pruritus | 14 | 0 | 3 | 0
Palmar-plantar Erythrodysesthesia Syndrome | 19 | 4 | 4 | <1
Skin Fissures | 19 | 2 | 1 | 0
a Adverse reactions occurring in ≥10% of patients in the cetuximab combination arm and at a higher incidence (≥5%) compared to the FOLFIRI alone arm.
b Adverse reactions were graded using the NCI CTC, version 2.0.
c Infusion reaction defined as any event meeting the medical concepts of allergy/anaphylaxis at any time during the clinical study or any event occurring on the first day of dosing and meeting the medical concepts of dyspnea and fever or by the following events: “acute myocardial infarction”, “angina pectoris”, “angioedema”, “autonomic seizure”, “blood pressure abnormal”, “blood pressure decreased”, “blood pressure increased”, “cardiac failure”, “cardiopulmonary failure”, “cardiovascular insufficiency”, “clonus”, “convulsion”, “coronary no-reflow phenomenon”, “epilepsy”, “hypertension”, “hypertensive crisis”, “hypertensive emergency”, “hypotension”, “infusion related reaction”, “loss of consciousness”, “myocardial infarction”, “myocardial ischemia”, “prinzmetal angina”, “shock”, “sudden death”, “syncope”, or “systolic hypertension”.
d Acne-like rash defined by the following events: “acne”, “acne pustular”, “butterfly rash”, “dermatitis acneiform”, “drug rash with eosinophilia and systemic symptoms”, “dry skin”, “erythema”, “exfoliative rash”, “folliculitis”, “genital rash”, “mucocutaneous rash”, “pruritus”, “rash”, “rash erythematous”, “rash follicular”, “rash generalized”, “rash macular”, “rash maculopapular”, “rash maculovesicular”, “rash morbilliform”, “rash papular”, “rash papulosquamous”, “rash pruritic”, “rash pustular”, “rash rubelliform”, “rash scarlatiniform”, “rash vesicular”, “skin exfoliation”, “skin hyperpigmentation”, “skin plaque”, “telangiectasia”, or “xerosis”.

As Single-Agent

The safety of ERBITUX with best supportive care (BSC) or BSC alone was evaluated in Study CA225-025. The data described below reflect exposure to ERBITUX in 242 patients with K-Ras wild-type, EGFR-expressing, metastatic colorectal cancer (mCRC) [see Warnings and Precautions (5.8)]. ERBITUX was administered intravenously at the recommended dosage (400 mg/m^2 initial dose, followed by 250 mg/m^2 weekly). Patients received a median of 17 infusions (range 1 to 51) [see Clinical Studies (14.2)].

Table 5 provides the frequency and severity of adverse reactions in Study CA225-025.

Table 5: Selected Adverse Reactions in ≥10% of Patients with K-Ras Wild-type, EGFR-expressing, Metastatic Colorectal Cancer Treated with Single-Agent ERBITUX (Study CA225-025)a
Adverse Reaction | ERBITUX with BSC (n=118) |  | BSC alone (n=124)
Adverse Reaction | Grades 1–4b | Grades 3 and 4 | Grades 1–4 | Grades 3 and 4
Dermatologic
Rash/Desquamation | 95 | 16 | 21 | 1
Dry Skin | 57 | 0 | 15 | 0
Pruritus | 47 | 2 | 11 | 0
Other-Dermatology | 35 | 0 | 7 | 2
Nail Changes | 31 | 0 | 4 | 0
General
Fatigue | 91 | 31 | 79 | 29
Fever | 25 | 3 | 16 | 0
Infusion Reactionsc | 18 | 3 | 0 | 0
Rigors, Chills | 16 | 1 | 3 | 0
Pain
Pain-Other | 59 | 18 | 37 | 10
Headache | 38 | 2 | 11 | 0
Bone Pain | 15 | 4 | 8 | 2
Pulmonary
Dyspnea | 49 | 16 | 44 | 13
Cough | 30 | 2 | 19 | 2
Gastrointestinal
Nausea | 64 | 6 | 50 | 6
Constipation | 53 | 3 | 38 | 3
Diarrhea | 42 | 2 | 23 | 2
Vomiting | 40 | 5 | 26 | 5
Stomatitis | 32 | 1 | 10 | 0
Other | 22 | 12 | 16 | 5
Dehydration | 13 | 5 | 3 | 0
Mouth Dryness | 12 | 0 | 6 | 0
Taste Disturbance | 10 | 0 | 5 | 0
Infection
Infection without neutropenia | 38 | 11 | 19 | 5
Musculoskeletal
Arthralgia | 14 | 3 | 6 | 0
Neurological
Neuropathy-sensory | 45 | 1 | 38 | 2
Insomnia | 27 | 0 | 13 | 0
Confusion | 18 | 6 | 10 | 2
Anxiety | 14 | 1 | 5 | 1
Depression | 14 | 0 | 5 | 0
a Adverse reactions occurring in ≥10% of patients in the ERBITUX with BSC arm and at a higher incidence (≥5%) compared to the BSC alone arm.
b Adverse reactions were graded using the NCI CTC, version 2.0.
c Infusion reaction defined as any event (chills, rigors, dyspnea, tachycardia, bronchospasm, chest tightness, swelling, urticaria, hypotension, flushing, rash, hypertension, nausea, angioedema, pain, sweating, tremors, shaking, drug fever, or other hypersensitivity reaction) recorded by the investigator as infusion-related.

In Combination with Irinotecan

ERBITUX at the recommended dosage was administered in combination with irinotecan in 354 patients with EGFR-expressing recurrent mCRC in Study CP02-9923 and BOND.

The most common adverse reactions were acneiform rash (88%), asthenia/malaise (73%), diarrhea (72%), and nausea (55%). The most common Grades 3–4 adverse reactions included diarrhea (22%), leukopenia (17%), asthenia/malaise (16%), and acneiform rash (14%).

BRAF V600E Mutation-Positive Metastatic Colorectal Cancer (CRC) in Combination with Encorafenib

The safety of ERBITUX (400 mg/m^2 initial dose, followed by 250 mg/m^2 weekly) in combination with encorafenib (300 mg once daily) was evaluated in 216 patients with BRAF V600E mutation-positive metastatic CRC in a randomized, open-label, active-controlled trial (BEACON CRC). The BEACON CRC trial [see Clinical Studies (14.3)] excluded patients with a history of Gilbert’s syndrome, abnormal left ventricular ejection fraction, prolonged QTc (>480 ms), uncontrolled hypertension, and history or current evidence of retinal vein occlusion. The median duration of exposure was 4.4 months for patients treated with ERBITUX in combination with encorafenib and 1.6 months for patients treated with either irinotecan or infusional 5-fluorouracil (5-FU)/folinic acid (FA)/irinotecan (FOLFIRI) in combination with ERBITUX.

The most common (≥ 25%) adverse reactions in patients receiving ERBITUX in combination with encorafenib were fatigue, nausea, diarrhea, dermatitis acneiform, abdominal pain, decreased appetite, arthralgia, and rash.

Table 6 and Table 7 present adverse drug reactions and laboratory abnormalities, respectively, identified in BEACON CRC.

Table 6: Adverse Reactions Occurring in ≥10% of Patients Receiving ERBITUX in Combination with Encorafenib in BEACON CRCa
Adverse Reaction | ERBITUX with encorafenib N=216 |  | ERBITUX with irinotecan or ERBITUX with FOLFIRI N=193
Adverse Reaction | All Grades (%) | ≥ Grade 3b (%) | All Grades (%) | ≥ Grade 3 (%)
General Disorders and Administration Site Conditions
Fatiguec | 51 | 7 | 50 | 8
Pyrexiac | 17 | 1 | 15 | 1
Gastrointestinal Disorders
Nausea | 34 | 1 | 41 | 1
Diarrheac | 33 | 2 | 48 | 10
Abdominal painc | 30 | 4 | 32 | 5
Vomiting | 21 | 1 | 29 | 3
Constipation | 15 | 0 | 18 | 1
Metabolism and Nutrition Disorders
Decreased appetite | 27 | 2 | 27 | 3
Musculoskeletal and Connective Tissue Disorders
Arthralgiac | 27 | 4 | 3 | 0
Myopathyc | 15 | 1 | 4 | 0
Pain in extremity | 10 | 0 | 1 | 0
Skin and Subcutaneous Tissue Disorders
Dermatitis acneiformc | 32 | 1 | 43 | 3
Rashc | 26 | 0 | 26 | 2
Pruritusc | 14 | 0 | 6 | 0
Melanocytic nevus | 14 | 0 | 0 | 0
Dry skinc | 13 | 0 | 12 | 1
Nervous System Disorders
Headachec | 20 | 0 | 3 | 0
Peripheral neuropathyc | 12 | 1 | 6 | 0
Vascular Disorders
Hemorrhagec | 19 | 2 | 9 | 0
Psychiatric Disorders
Insomniac | 13 | 0 | 6 | 0
a Grades per National Cancer Institute CTCAE v4.03.
b Grade 4-5 adverse reactions in the ERBITUX with encorafenib arm were limited to Grade 5 hemorrhage (n=1).
c Represents a composite of multiple, related preferred terms.

Other clinically important adverse reactions occurring in <10% of patients who received ERBITUX in combination with encorafenib were:

Gastrointestinal disorders: Pancreatitis

Table 7: Laboratory Abnormalities Occurring in ≥10% (All Grades) of Patients Receiving ERBITUX in Combination with Encorafenib in BEACON CRCa
Laboratory Abnormalityb | ERBITUX with encorafenib |  | ERBITUX with irinotecan or ERBITUX with FOLFIRI
Laboratory Abnormalityb | All Grades (%)bb | Grades 3 and 4 (%) | All Grades (%) | Grades 3 and 4 (%)
Hematology
Anemia | 34 | 4 | 48 | 5
Lymphopenia | 24 | 7 | 35 | 5
Increased Activated Partial Thromboplastin Time | 13 | 1 | 7 | 1
Chemistry
Hypomagnesemia | 19 | 0 | 22 | 1
Increased Alkaline Phosphatase | 18 | 4 | 30 | 7
Increased ALT | 17 | 0 | 29 | 3
Increased AST | 15 | 1 | 22 | 2
Hypokalemia | 12 | 3 | 32 | 5
Hyponatremia | 11 | 2 | 13 | 2
a Grades per National Cancer Institute CTCAE v4.03.
b Based on the number of patients with available baseline and at least one on-treatment laboratory test.

6.2 Immunogenicity

As with all therapeutic proteins, there is potential for immunogenicity. The detection of antibody formation is highly dependent on the sensitivity and specificity of the assay. Additionally, the observed incidence of antibody (including neutralizing antibody) positivity in an assay may be influenced by several factors including assay methodology, sample handling, timing of sample collection, concomitant medications, and underlying disease. For these reasons, comparison of the incidence of antibodies to cetuximab in the studies below with the incidence of antibodies to cetuximab in other studies or to other products may be misleading.

An ELISA methodology was used to characterize the incidence of anti-cetuximab antibodies. The incidence of anti-cetuximab binding antibodies in 105 patients (from studies I4E-MC-JXBA, I4E-MC-JXBB, and I4E-MC-JXBD) with at least one post-baseline blood sample (≥4 weeks post first ERBITUX administration) was <5%.

6.3 Postmarketing Experience

The following adverse reactions have been identified during post approval use of ERBITUX. Because these reactions are reported voluntarily from a population of uncertain size, it is not always possible to reliably estimate their frequency or establish a causal relationship to drug exposure.

- Neurologic: Aseptic meningitis
- Gastrointestinal: Mucosal inflammation
- Dermatologic: Stevens-Johnson syndrome, toxic epidermal necrolysis, life-threatening and fatal bullous mucocutaneous disease

8 USE IN SPECIFIC POPULATIONS

8.1 Pregnancy

Risk Summary

Based on findings from animal studies and its mechanism of action [see Clinical Pharmacology (12.1)], ERBITUX can cause fetal harm when administered to a pregnant woman. There are no available data for ERBITUX exposure in pregnant women. In an animal reproduction study, intravenous administration of cetuximab once weekly to pregnant cynomolgus monkeys during the period of organogenesis resulted in an increased incidence of embryolethality and abortion. Disruption or depletion of EGFR in animal models results in impairment of embryo-fetal development including effects on placental, lung, cardiac, skin, and neural development (see Data). Human IgG is known to cross the placental barrier; therefore, cetuximab may be transmitted from the mother to the developing fetus. Advise pregnant women of the potential risk to a fetus.

In the U.S. general population, the estimated background risk of major birth defects and miscarriage in clinically recognized pregnancies is 2 to 4% and 15 to 20% respectively.

Data

Animal Data

Pregnant cynomolgus monkeys were administered cetuximab intravenously once weekly during the period of organogenesis (gestation day [GD] 20-48) at dose levels 0.4 to 4 times the recommended dose of ERBITUX based on body surface area (BSA). Cetuximab was detected in the amniotic fluid and in the serum of embryos from treated dams on GD 49. While no fetal malformations occurred in offspring, there was an increased incidence of embryolethality and abortions at doses approximately 1 to 4 times the recommended dose of ERBITUX based on BSA.

In mice, EGFR is critically important in reproductive and developmental processes including blastocyst implantation, placental development, and embryo-fetal/postnatal survival and development. Reduction or elimination of embryo-fetal or maternal EGFR signaling can prevent implantation, can cause embryo-fetal loss during various stages of gestation (through effects on placental development), and can cause developmental anomalies and early death in surviving fetuses. Adverse developmental outcomes were observed in multiple organs in embryos/neonates of mice with disrupted EGFR signaling.

8.2 Lactation

Risk Summary

There is no information regarding the presence of ERBITUX in human milk, the effects on the breastfed infant, or the effects on milk production. Human IgG antibodies can be excreted in human milk. Due to the potential for serious adverse reactions in breastfed infants from ERBITUX, advise women not to breastfeed during treatment with ERBITUX and for 2 months after the last dose of ERBITUX.

8.3 Females and Males of Reproductive Potential

Pregnancy Testing

Verify pregnancy status in females of reproductive potential prior to initiating ERBITUX [see Use in Specific Population (8.1)].

Contraception

Based on its mechanism of action, ERBITUX can cause harm to the fetus when administered to a pregnant woman [see Use in Specific Populations (8.1)].

Females

Advise females of reproductive potential to use effective contraception during treatment with ERBITUX and for 2 months after the last dose of ERBITUX.

Infertility

Females

Based on animal studies, ERBITUX may impair fertility in females of reproductive potential [see Nonclinical Toxicology (13.1)].

8.4 Pediatric Use

The safety and effectiveness of ERBITUX in pediatric patients have not been established. The pharmacokinetics of cetuximab, in combination with irinotecan, were evaluated in pediatric patients with refractory solid tumors in an open-label, single-arm, dose-finding study. ERBITUX was administered once-weekly, at doses up to 250 mg/m^2, to 27 patients ranging from 1 to 12 years old; and in 19 patients ranging from 13 to 18 years old. No new safety signals were identified in pediatric patients. The pharmacokinetics of cetuximab between the two age groups were similar following a single dose of 75 mg/m^2 and 150 mg/m^2. The volume of the distribution appears to be independent of dose and approximates the vascular space of 2 L/m^2 to 3 L/m^2. Following a single dose of 250 mg/m^2, the mean AUC0-inf (CV%) was 17.7 mg*h/mL (34%) in the younger age group (1–12 years, n=9) and 13.4 mg*h/mL (38%) in the adolescent group (13–18 years, n=6). The mean half-life of cetuximab was 110 hours (69 to 188 hours) in the younger group and 82 hours (55 to 117 hours) in the adolescent group.

8.5 Geriatric Use

Of the 1662 patients with advanced colorectal cancer who received ERBITUX with irinotecan, with FOLFIRI or as single-agent in six studies (BOND, IMCL-CP02-9923, IMCL-CP02-0141, IMCL-CP02-0144, CA225-025 and CRYSTAL), 35% of patients were 65 years of age or older. No overall differences in safety or efficacy were observed between these patients and younger patients.

Clinical studies of ERBITUX conducted in patients with head and neck cancer did not include sufficient number of subjects aged 65 and over to determine whether they respond differently from younger subjects.

Of the 216 patients with BRAF V600E mutation positive metastatic CRC who received ERBITUX in combination with encorafenib 300 mg, once daily, 29% were 65 years of age to up to 75 years of age, while 20 (9%) were 75 years of age and over [see Clinical Studies (14.3)].

No overall differences in the safety or effectiveness of ERBITUX plus encorafenib were observed in elderly patients as compared to younger patients.

11 DESCRIPTION

Cetuximab is an epidermal growth factor receptor (EGFR) antagonist. It is a recombinant, human/mouse chimeric monoclonal antibody that binds specifically to the extracellular domain of the human epidermal growth factor receptor (EGFR). Cetuximab is composed of the Fv regions of a murine anti-EGFR antibody with human IgG1 heavy and kappa light chain constant regions and has an approximate molecular weight of 152 kDa. Cetuximab is produced in mammalian (murine myeloma) cell culture.

ERBITUX (cetuximab) injection for intravenous use, is a sterile, preservative-free, clear, colorless solution, which may contain a small amount of visible, white, amorphous cetuximab particulates in a single-dose vial. Each 1 mL of solution contains 2 mg of cetuximab, sodium chloride (8.48 mg), sodium phosphate dibasic heptahydrate (1.88 mg), sodium phosphate monobasic monohydrate (0.41 mg), and Water for Injection, USP at pH of 7.0 to 7.4.

12 CLINICAL PHARMACOLOGY

12.1 Mechanism of Action

The epidermal growth factor receptor (EGFR, HER1, c-ErbB-1) is a transmembrane glycoprotein that is a member of a subfamily of type I receptor tyrosine kinases including EGFR, HER2, HER3, and HER4. The EGFR is constitutively expressed in many normal epithelial tissues, including the skin and hair follicle. Expression of EGFR is also detected in many human cancers including those of the head and neck, colon, and rectum.

Cetuximab binds specifically to the EGFR on both normal and tumor cells, and competitively inhibits the binding of epidermal growth factor (EGF) and other ligands, such as transforming growth factor-alpha. In vitro assays and in vivo animal studies have shown that binding of cetuximab to the EGFR blocks phosphorylation and activation of receptor-associated kinases, resulting in inhibition of cell growth, induction of apoptosis, and decreased matrix metalloproteinase and vascular endothelial growth factor production. Signal transduction through the EGFR results in activation of wild-type Ras proteins, but in cells with activating Ras somatic mutations, the resulting mutant Ras proteins are continuously active regardless of EGFR regulation.

In vitro, cetuximab can mediate antibody-dependent cellular cytotoxicity (ADCC) against certain human tumor types. In vitro assays and in vivo animal studies have shown that cetuximab inhibits the growth and survival of tumor cells that express the EGFR. No anti-tumor effects of cetuximab were observed in human tumor xenografts lacking EGFR expression. The addition of cetuximab to radiation therapy or irinotecan in human tumor xenograft models in mice resulted in an increase in anti-tumor effects compared to radiation therapy or chemotherapy alone.

In the setting of BRAF-mutant CRC, induction of EGFR-mediated MAPK pathway activation has been identified as a mechanism of resistance to BRAF inhibitors. Combinations of a BRAF inhibitor and agents targeting EGFR have been shown to overcome this resistance mechanism in nonclinical models. Coadministration of cetuximab and encorafenib had an anti-tumor effect greater than either drug alone, in a mouse model of colorectal cancer with mutated BRAF V600E.

12.3 Pharmacokinetics

ERBITUX administered as a single-agent or in combination with concomitant chemotherapy or radiation therapy exhibits nonlinear pharmacokinetics. The area under the concentration time curve (AUC) increased in a greater than dose proportional manner while clearance of cetuximab decreased from 0.08 L/h/m^2 to 0.02 L/h/m^2 as the dose increased from 20 mg/m^2 to 200 mg/m^2 and plateaued at doses >200 mg/m^2.

The systemic exposure of cetuximab after ERBITUX administration was 22% (90% CI: 6%, 38%) higher than that of another cetuximab product used in EXTREME and CRYSTAL.

Distribution

The volume of the distribution for cetuximab appeared to be independent of dose and approximated the vascular space of 2–3 L/m^2.

Elimination

Following the recommended dosage (400 mg/m^2 initial dose; 250 mg/m^2 weekly dose), concentrations of cetuximab reached steady-state levels by the third weekly infusion with mean peak and trough concentrations across studies ranging from 168 μg/mL to 235 μg/mL and 41 μg/mL to 85 μg/mL, respectively. The mean half-life of cetuximab was approximately 112 hours (63 to 230 hours).

Specific Population

Age, sex, race, hepatic and renal function had no clinically significant effect on the pharmacokinetics of cetuximab. Clearance of cetuximab increased 1.8-fold as body surface area increased from 1.3 m^2 to 2.3 m^2, which is consistent with the recommended dosing of cetuximab on mg/m^2 basis.

Drug Interaction Studies

No pharmacokinetic interaction was observed between cetuximab and irinotecan, cetuximab and cisplatin, and cetuximab and carboplatin.

No clinically significant differences in the pharmacokinetics of cetuximab or encorafenib were observed when the recommended ERBITUX initial dose of 400 mg/m^2 was co-administered with encorafenib.

13 NONCLINICAL TOXICOLOGY

13.1 Carcinogenesis, Mutagenesis, Impairment of Fertility

Long-term animal studies have not been performed to test cetuximab for carcinogenic potential, and no mutagenic or clastogenic potential of cetuximab was observed in the Salmonella-Escherichia coli (Ames) assay or in the in vivo rat micronucleus test. Menstrual cyclicity was impaired in female cynomolgus monkeys receiving weekly doses of 0.4 to 4 times the recommended dose of ERBITUX (based on total body surface area). Cetuximab-treated animals exhibited increased incidences of irregular or absent cycles, as compared to control animals. These effects were initially noted beginning on week 25 and continued through the 6-week recovery period. No effects of cetuximab were observed on measured male fertility parameters (i.e., serum testosterone levels and analysis of sperm counts, viability, and motility) as compared to control male monkeys.

14 CLINICAL STUDIES

14.1 Squamous Cell Carcinoma of the Head and Neck (SCCHN)

In Combination with Radiation Therapy

BONNER (NCT00004227) was a randomized, multicenter, controlled trial of 424 patients with locally or regionally advanced SCCHN. Patients with Stage III/IV SCCHN of the oropharynx, hypopharynx, or larynx with no prior therapy were randomized (1:1) to receive either ERBITUX in combination with radiation therapy or radiation therapy alone. Stratification factors were Karnofsky performance status (60–80 versus 90–100), nodal stage (N0 versus N+), tumor stage (T1–3 versus T4 using American Joint Committee on Cancer 1998 staging criteria), and radiation therapy fractionation (concomitant boost versus once-daily versus twice-daily). Radiation therapy was administered for 6–7 weeks as once-daily, twice-daily, or concomitant boost. ERBITUX was administered intravenously as a 400 mg/m^2 initial dose beginning one week prior to initiation of radiation therapy, followed by 250 mg/m^2 weekly administered 1 hour prior to radiation therapy for the duration of radiation therapy (6–7 weeks). The main efficacy outcome measure was duration of locoregional control. Another outcome measure was overall survival (OS).

Of the 424 randomized patients, the median age was 57 years, 80% were male, 83% were White, and 90% had baseline Karnofsky performance status ≥80. There were 258 patients enrolled in U.S. sites (61%). Sixty percent of patients had oropharyngeal, 25% laryngeal, and 15% hypopharyngeal primary tumors; 28% had AJCC T4 tumor stage. Fifty-six percent of the patients received radiation therapy with concomitant boost, 26% received once-daily regimen, and 18% twice-daily regimen.

Efficacy results are presented in Table 8.

Table 8: Efficacy Results in Locoregionally Advanced SCCHN in BONNER
 | ERBITUX plus Radiation (n=211) | Radiation Alone (n=213) | Hazard Ratio (95% CIa) | Stratified Log-rank p-value
Locoregional Control
Median duration (months) | 24.4 | 14.9 | 0.68 (0.52–0.89) | 0.005
Overall Survival
Median duration (months) | 49.0 | 29.3 | 0.74 (0.57–0.97) | 0.03
a CI = confidence interval.

In Combination with Platinum-based Therapy with Fluorouracil

EXTREME (NCT00122460) was an open-label, randomized, multicenter, controlled trial of 442 patients with recurrent locoregional disease or metastatic SCCHN. Patients with no prior therapy for recurrent locoregional disease or metastatic SCCHN were randomized (1:1) to receive a cetuximab product in combination with platinum-based therapy and fluorouracil or platinum-based therapy and fluorouracil alone. Choice of cisplatin or carboplatin was at the discretion of the investigator. Stratification factors were Karnofsky performance status (<80 versus ≥80) and previous chemotherapy. Cisplatin (100 mg/m^2 intravenously on Day 1) or carboplatin (AUC 5 mg/mL*min intravenously on Day 1) and fluorouracil (1000 mg/m^2/day intravenously on Days 1–4) were administered every 3 weeks (1 cycle) for a maximum of 6 cycles in the absence of disease progression or unacceptable toxicity. Cetuximab was administered intravenously at a 400 mg/m^2 initial dose, followed by a 250 mg/m^2 weekly dose. In the absence of disease progression or unacceptable toxicity after completion of 6 planned courses of platinum-based therapy, weekly cetuximab as a single-agent could be continued until disease progression or unacceptable toxicity. If chemotherapy was delayed because of adverse reactions, weekly cetuximab was continued. If chemotherapy was discontinued for adverse reactions, weekly cetuximab as a single-agent could be continued until disease progression or unacceptable toxicity. The main efficacy outcome measure was OS. Other outcome measures were PFS and objective response rate (ORR).

Of the 442 randomized patients, the median age was 57 years, 90% were male, 98% were White, and 88% had baseline Karnofsky performance status ≥80. Thirty-four percent of patients had oropharyngeal, 25% laryngeal, 20% oral cavity, and 14% hypopharyngeal primary tumors. Fifty-three percent of patients had recurrent locoregional disease only and 47% had metastatic disease. Fifty-eight percent had AJCC Stage IV disease and 21% had Stage III disease. Sixty-four percent of patients received cisplatin therapy and 34% received carboplatin as initial therapy. Approximately fifteen percent of the patients in the cisplatin alone arm switched to carboplatin during the treatment period.

Efficacy results are presented in Table 9 and Figure 1.

Table 9: Efficacy Results in Recurrent Locoregional Disease or Metastatic SCCHN in EXTREME
 | Cetuximab with Platinum-based Therapy and Fluorouracil (n=222) | Platinum-based Therapy and Fluorouracil (n=220)
Overall Survival
Median Duration (months) | 10.1 | 7.4
Hazard Ratio (95% CIa) | 0.80 (0.64, 0.98)
Stratified Log-rank p-value | 0.034
Progression-free Survival
Median Duration (months) | 5.5 | 3.3
Hazard Ratio (95% CIa) | 0.57 (0.46, 0.72)
Stratified Log-rank p-value | <0.0001
Objective Response Rate | 35.6% | 19.5%
Odds Ratio (95% CIa) | 2.33 (1.50, 3.60)
CMHb Test p-value | 0.0001
a CI = confidence interval.
b CMH = Cochran-Mantel-Haenszel.

Figure 1: Kaplan-Meier Curves for Overall Survival in Patients with Recurrent Locoregional Disease or Metastatic SCCHN in EXTREME

CT = Platinum-based therapy with fluorouracil

CET = another cetuximab product

In exploratory subgroup analyses by initial platinum therapy (cisplatin or carboplatin), for patients (N=284) receiving cetuximab in combination with cisplatin and fluorouracil compared to cisplatin and fluorouracil alone, the difference in median OS was 3.3 months (10.6 versus 7.3 months; HR 0.71; 95% CI 0.54, 0.93). The difference in median PFS was 2.1 months (5.6 versus 3.5 months; HR 0.55; 95% CI 0.41, 0.73). The ORR was 39% and 23%, respectively (OR 2.18; 95% CI 1.29, 3.69).

For patients (N=149) receiving cetuximab in combination with carboplatin and fluorouracil compared to carboplatin and fluorouracil alone, the difference in median OS was 1.4 months (9.7 versus 8.3 months; HR 0.99; 95% CI 0.69, 1.43). The difference in median PFS was 1.7 months (4.8 versus 3.1 months, respectively; HR 0.61; 95% CI 0.42, 0.89). The ORR was 30% and 15%, respectively (OR 2.45; 95% CI 1.10, 5.46).

As Single-Agent

EMR 62202-016 was a single-arm, multicenter clinical trial in 103 patients with recurrent or metastatic SCCHN. All patients had documented disease progression within 30 days of a platinum-based chemotherapy regimen. Patients were administered intravenously a 20-mg test dose of ERBITUX on Day 1, followed by a 400 mg/m^2 initial dose, and 250 mg/m^2 weekly until disease progression or unacceptable toxicity.

The median age was 57 years, 82% were male, 100% White, and 62% had a Karnofsky performance status of ≥80.

The ORR was 13% (95% CI 7%, 21%). Median duration of response (DoR) was 5.8 months (range 1.2 to 5.8 months).

14.2 K-Ras Wild-type, EGFR-expressing, Metastatic Colorectal Cancer (CRC)

In Combination with FOLFIRI

CRYSTAL (NCT00154102) was a randomized, open-label, multicenter, study of 1217 patients with EGFR-expressing, mCRC. Patients were randomized (1:1) to receive either a cetuximab product in combination with FOLFIRI or FOLFIRI alone as first-line treatment. Stratification factors were Eastern Cooperative Oncology Group (ECOG) performance status (0 and 1 versus 2) and region (Western Europe versus Eastern Europe versus other).

FOLFIRI regimen included 14-day cycles of irinotecan (180 mg/m^2 intravenously on Day 1), folinic acid (400 mg/m^2 [racemic] or 200 mg/m^2 [L-form] intravenously on Day 1), and fluorouracil (400 mg/m^2 bolus on Day 1 followed by 2400 mg/m^2 as a 46-hour continuous infusion). Cetuximab was administered intravenously as a 400 mg/m^2 initial dose , followed by 250 mg/m^2 weekly administered 1 hour prior to chemotherapy. Study treatment continued until disease progression or unacceptable toxicity. The main efficacy outcome measure was PFS assessed by an independent review committee (IRC). Other outcome measures were OS and ORR.

Of the 1217 randomized patients, the median age was 61 years, 60% were male, 86% were White, and 96% had a baseline ECOG performance status 0–1, 60% had primary tumor localized in colon, 84% had 1–2 metastatic sites and 20% had received prior adjuvant and/or neoadjuvant chemotherapy. Demographics and baseline characteristics were similar between study arms.

K-Ras mutation status was available for 89% of the patients: 63% had K-Ras wild-type tumors and 37% had K-Ras mutant tumors where testing assessed for the following somatic mutations in codons 12 and 13 (exon 2): G12A, G12D, G12R, G12C, G12S, G12V, G13D. Baseline characteristics and demographics in the K-Ras wild-type subset were similar to that seen in the overall population.

A statistically significant improvement in PFS was observed for the cetuximab with FOLFIRI arm compared with the FOLFIRI arm (median PFS 8.9 vs. 8.1 months, HR 0.85 [95% CI 0.74, 0.99], p-value=0.036). OS was not significantly different at the planned, final analysis based on 838 events (HR=0.93, 95% CI [0.8, 1.1], p-value 0.327).

Results of the planned PFS and ORR analysis in all randomized patients and post-hoc PFS and ORR analysis in subgroups of patients defined by K-Ras mutation status, and post-hoc analysis of updated OS based on additional follow-up (1000 events) in all randomized patients and in subgroups of patients defined by K-Ras mutation status are presented in Table 10 and Figure 2. The treatment effect in the all-randomized population for PFS was driven by treatment effects limited to patients who have K-Ras wild-type tumors. There is no evidence of effectiveness in the subgroup of patients with K-Ras mutant tumors.

Table 10: Efficacy Results in First-line EGFR-expressing, Metastatic Colorectal Cancer in CRYSTAL (All Randomized and K-Ras Status)
 | All Randomized |  | K-Ras Wild-type |  | K-Ras Mutant
 | Cetuximab with FOLFIRI (n=608) | FOLFIRI (n=609) | Cetuximab with FOLFIRI (n=320) | FOLFIRI (n=356) | Cetuximab with FOLFIRI (n=216) | FOLFIRI (n=187)
Progression-Free Survival
Number of Events (%) | 343 (56) | 371 (61) | 165 (52) | 214 (60) | 138 (64) | 112 (60)
Median (months) (95% CI) | 8.9 (8.0, 9.4) | 8.1 (7.6, 8.8) | 9.5 (8.9, 11.1) | 8.1 (7.4, 9.2) | 7.5 (6.7, 8.7) | 8.2 (7.4, 9.2)
HR (95% CI) | 0.85 (0.74, 0.99) |  | 0.70 (0.57, 0.86) |  | 1.13 (0.88, 1.46)
p-valuea | 0.0358
Overall Survivalb
Number of Events (%) | 491 (81) | 509 (84) | 244 (76) | 292 (82) | 189 (88) | 159 (85)
Median (months) (95% CI) | 19.6 (18, 21) | 18.5 (17, 20) | 23.5 (21, 26) | 19.5 (17, 21) | 16.0 (15, 18) | 16.7 (15, 19)
HR (95% CI) | 0.88 (0.78, 1.0) |  | 0.80 (0.67, 0.94) |  | 1.04 (0.84, 1.29)
Objective Response Rate
ORR (95% CI) | 46% (42, 50) | 38% (34, 42) | 57% (51, 62) | 39% (34, 44) | 31% (25, 38) | 35% (28, 43)
a Based on the Stratified Log-rank test.
b Post-hoc updated OS analysis, results based on an additional 162 events.

Figure 2: Kaplan-Meier Curves for Overall Survival in the K-Ras Wild-type Population in CRYSTAL

As Single-Agent

Study CA225-025 (NCT00079066) was a multicenter, open-label, randomized, clinical trial conducted in 572 patients with EGFR-expressing, previously treated, recurrent mCRC. Patients were randomized (1:1) to receive either ERBITUX with best supportive care (BSC) or BSC alone. ERBITUX was administered intravenously as a 400 mg/m^2 initial dose, followed by 250 mg/m^2 weekly until disease progression or unacceptable toxicity. The main efficacy outcome measure was OS.

Of the 572 randomized patients, the median age was 63 years, 64% were male, 89% were White, and 77% had baseline ECOG performance status of 0–1. Demographics and baseline characteristics were similar between study arms. All patients were to have received and progressed on prior therapy including an irinotecan-containing regimen and an oxaliplatin-containing regimen.

K-Ras status was available for 79% of the patients: 54% had K-Ras wild-type tumors and 46% had K-Ras mutant tumors where testing assessed for the following somatic mutations in codons 12 and 13 (exon 2): G12A, G12D, G12R, G12C, G12S, G12V, G13D.

Efficacy results are presented in Table 11 and Figure 3.

Table 11: Overall Survival in Previously Treated EGFR-expressing, Metastatic Colorectal Cancer in Study CA225-025 (All Randomized and K-Ras Status)
 | All Randomized |  | K-Ras Wild-type |  | K-Ras Mutant
 | ERBITUX with BSC (N=287) | BSC (N=285) | ERBITUX with BSC (N=117) | BSC (N=128) | ERBITUX with BSC (N=108) | BSC (N=100)
Median (months) (95% CI) | 6.1 (5.4, 6.7) | 4.6 (4.2, 4.9) | 8.6 (7.0, 10.3) | 5.0 (4.3, 5.7) | 4.8 (3.9, 5.6) | 4.6 (3.6, 4.9)
HR (95% CI) | 0.77 (0.64, 0.92) |  | 0.63 (0.47, 0.84) |  | 0.91 (0.67, 1.24)
p-valuea | 0.0046
a Based on the Stratified Log-rank test.

Figure 3: Kaplan-Meier Curves for Overall Survival in Patients with K-Ras Wild-type Metastatic Colorectal Cancer in Study CA225-025

In Combination with Irinotecan

BOND was a multicenter, clinical trial conducted in 329 patients with EGFR-expressing recurrent mCRC. Tumor specimens were not available for testing for K-Ras mutation status. Patients were randomized (2:1) to receive either ERBITUX in combination with irinotecan (218 patients) or ERBITUX single-agent (111 patients). ERBITUX was administered intravenously as a 400 mg/m^2 initial dose, followed by 250 mg/m^2 weekly until disease progression or unacceptable toxicity. In the ERBITUX with irinotecan arm, irinotecan was added to ERBITUX using the same dosage for irinotecan as the patient had previously failed. Acceptable irinotecan schedules were 350 mg/m^2 every 3 weeks, 180 mg/m^2 every 2 weeks, or 125 mg/m^2 weekly times four doses every 6 weeks. The efficacy of ERBITUX with irinotecan or ERBITUX single-agent, based on durable objective responses, was evaluated in all randomized patients and in two pre-specified subpopulations: irinotecan refractory and irinotecan and oxaliplatin failures.

Of the 329 patients, the median age was 59 years, 63% were male, 98% were White, and 88% had baseline Karnofsky performance status ≥80. Approximately two-thirds had previously failed oxaliplatin treatment.

In patients receiving ERBITUX with irinotecan, the ORR was 23% (95% CI 18%, 29%), median DoR was 5.7 months, and median time to progression was 4.1 months. In patients receiving ERBITUX as a single-agent, the ORR was 11% (95% CI 6%, 18%), median DoR was 4.2 months, and median time to progression was 1.5 months. Similar response rates were observed in the pre-defined subsets in both the combination arm and single-agent arm.

14.3 BRAF V600E Mutation-Positive Metastatic Colorectal Cancer (CRC)

ERBITUX in combination with encorafenib was evaluated in a randomized, active-controlled, open label, multicenter trial (BEACON CRC; NCT02928224). Eligible patients were required to have BRAF V600E mutation-positive metastatic CRC, as detected using the Qiagen therascreen BRAF V600E RGQ polymerase chain reaction (PCR) Kit, with disease progression after 1 or 2 prior regimens. Other key eligibility criteria included absence of prior treatment with a RAF, MEK, or EGFR inhibitor, eligibility to receive cetuximab per local labeling with respect to tumor RAS status, and ECOG performance status (PS) 0–1. Randomization was stratified by ECOG performance status (0 versus 1), prior use of irinotecan (yes versus no), and cetuximab product used (US-licensed versus EU-approved).

Patients were randomized 1:1:1 to one of the following treatment arms:

- ERBITUX in combination with encorafenib 300 mg orally once daily (ERBITUX/encorafenib arm)
- ERBITUX in combination with binimetinib and encorafenib 300 mg orally once daily
- ERBITUX with irinotecan or ERBITUX with FOLFIRI (control arm)

The dosage of cetuximab in all patients was 400 mg/m^2 intravenously for the first dose followed by 250 mg/m^2 weekly.

Patients in the control arm received ERBITUX with either irinotecan 180 mg/m^2 intravenously on Days 1 and 15 of each 28-day cycle or FOLFIRI intravenously (irinotecan 180 mg/m^2 on Days 1 and 15; folinic acid 400 mg/m^2 on Days 1 and 15; then fluorouracil 400 mg/m^2 bolus on Days 1 and 15 followed by fluorouracil 2400 mg/m^2 /day by continuous infusion over 2 days).

Treatment continued until disease progression or unacceptable toxicity. Only the results of the approved regimen (ERBITUX in combination with encorafenib) are described below.

The major efficacy outcome measure was OS. Additional efficacy outcome measures included PFS, ORR, and DoR as assessed by blinded independent central review (BICR). OS and PFS were assessed in all randomized patients. ORR and DoR were assessed in the subset of the first 220 patients included in the randomized portion of the ERBITUX/encorafenib and control arm of the study.

A total of 220 patients were randomized to the ERBITUX/encorafenib arm and 221 to the control arm. Of these 441 patients, the median age was 61 years; 53% were female; 80% were White and 15% were Asian. Fifty percent (50%) had baseline ECOG performance status of 0; 66% received 1 prior therapy and 34% received 2; 93% received prior oxaliplatin and 52% received prior irinotecan.

ERBITUX in combination with encorafenib demonstrated a statistically significant improvement in OS, ORR, and PFS compared to the active comparator. Efficacy results are summarized in Table 12 and Figure 4.

Table 12: Efficacy Results in BRAF V600E Mutation-Positive Metastatic Colorectal Cancer in BEACON CRC
 | ERBITUX with encorafenib N=220 | ERBITUX with irinotecan or ERBITUX with FOLFIRI N=221
 | Overall Survival
Number of Events (%) | 93 (42) | 114 (52)
Median OS, months (95% CI) | 8.4 (7.5, 11.0) | 5.4 (4.8, 6.6)
HR (95% CI)a,b | 0.60 (0.45, 0.79)
p-valuea,c | 0.0003
Overall Response Rate (per BICR)
ORR (95% CI)d | 20% (13%, 29%) | 2% (0%, 7%)
CR | 5% | 0%
PR | 15% | 2%
p-valuea,e | <0.0001
Median DoR, months (95% CI) | 6.1 (4.1, 8.3) | NR (2.6, NR)
Progression Free Survival (per BICR)
Number of events (%) | 133 (60) | 128 (58)
Progressive disease | 110 (50) | 101 (46)
Death | 23 (10) | 27 (12)
Median PFS, months (95% CI) | 4.2 (3.7, 5.4) | 1.5 (1.4, 1.7)
HR (95% CI)a,b | 0.40 (0.31, 0.52)
p-valuea,f | <0.0001
CI = Confidence interval; CR = Complete response; DoR = Duration of response; HR = Hazard ratio; NR = Not reached; ORR = Overall response rate; OS = Overall survival; PFS = Progression-free survival; PR = Partial response.
a Stratified by ECOG PS, source of cetuximab (US-licensed versus EU-approved) and prior irinotecan use at randomization.
b Stratified Cox proportional hazard model.
c Stratified log-rank test, tested at alpha level of 0.0084.
d ERBITUX/encorafenib arm (n=113) and control arm (n=107).
e Cochran-Mantel-Haenszel test; tested at alpha level of 0.05.
f Stratified log-rank test, tested at alpha level of 0.0234.

Figure 4: Kaplan-Meier Curves for Overall Survival in Patients with BRAF V600E Mutation-Positive Metastatic Colorectal Cancer in BEACON

16 HOW SUPPLIED/STORAGE AND HANDLING

How Supplied

ERBITUX® (cetuximab) injection is a sterile, preservative-free, clear, colorless solution in a 2 mg/mL single-dose vial supplied as follows:

- 100 mg/50 mL individually packaged in a carton (NDC 66733-948-23)
- 200 mg/100 mL individually packaged in a carton (NDC 66733-958-23)

Storage and Handling

- Store vials under refrigeration at 2° C to 8° C (36° F to 46° F).
- Do not freeze or shake.
- Increased particulate formation may occur at temperatures at or below 0° C (32° F).
- Discard any remaining solution in the infusion container after 8 hours at controlled room temperature or after 12 hours at 2° C to 8° C.
- Discard any unused portion of the vial.

17 PATIENT COUNSELING INFORMATION

Infusion Reactions

Advise patients that the risk of serious infusion reactions may be increased in patients who have had a tick bite or red meat allergy. Advise patients to contact their healthcare provider and to report signs and symptoms of infusion reactions, including late onset infusion reactions, such as fever, chills, or breathing problems [see Warnings and Precautions (5.1)].

Cardiopulmonary Arrest

Advise patients of the risk of cardiopulmonary arrest or sudden death and to report any history of coronary artery disease, congestive heart failure, or arrhythmias [see Warnings and Precautions (5.2)].

Pulmonary Toxicity

Advise patients to contact their healthcare provider immediately for new or worsening cough, chest pain, or shortness of breath [see Warnings and Precautions (5.3)].

Dermatologic Toxicities

Advise patients to limit sun exposure during ERBITUX treatment and for 2 months after the last dose of ERBITUX. Advise patients to notify their healthcare provider of any sign of acne-like rash, (which can include itchy, dry, scaly, or cracking skin and inflammation, infection or swelling at the base of the nails or loss of the nails), conjunctivitis, blepharitis, or decreased vision [see Warnings and Precautions (5.4)].

Embryo-Fetal Toxicity

Advise female patients of reproductive potential of the potential risk to a fetus and to use effective contraception during ERBITUX treatment and for 2 months after the last dose of ERBITUX. Advise patients to inform their healthcare provider of a known or suspected pregnancy [see Warnings and Precautions (5.8), Use in Specific Populations (8.3)].

Lactation

Advise patients not to breastfeed during ERBITUX treatment and for 2 months after the last dose of ERBITUX [see Use in Specific Populations (8.2)].

ERBITUX® is a registered trademark of ImClone LLC a wholly-owned subsidiary of Eli Lilly and Company.

Manufactured by ImClone LLC a wholly-owned subsidiary of Eli Lilly and Company, Branchburg, NJ 08876 USA

Eli Lilly and Company, Indianapolis, IN 46285, USA
US License No. 1827

Copyright © 2004, 2021, ImClone LLC a wholly-owned subsidiary of Eli Lilly and Company. All rights reserved.

ERB-0009-USPI-20210927

PACKAGE LABEL

PACKAGE LABEL- Erbitux 50 mL (2mg/mL) Vial Carton

NDC 66733-948-23

ERBITUX®

CETUXIMAB

Injection

For intravenous use

Rx only

100 mg/50 mL

(2 mg/mL)

DO NOT DILUTE

Lilly

PACKAGE LABEL

PACKAGE LABEL- Erbitux 100 mL (2mg/mL) Vial Carton

NDC 66733-958-23

ERBITUX®

CETUXIMAB

Injection

For intravenous use

Rx only

200 mg/100 mL

(2 mg/mL)

DO NOT DILUTE

Lilly